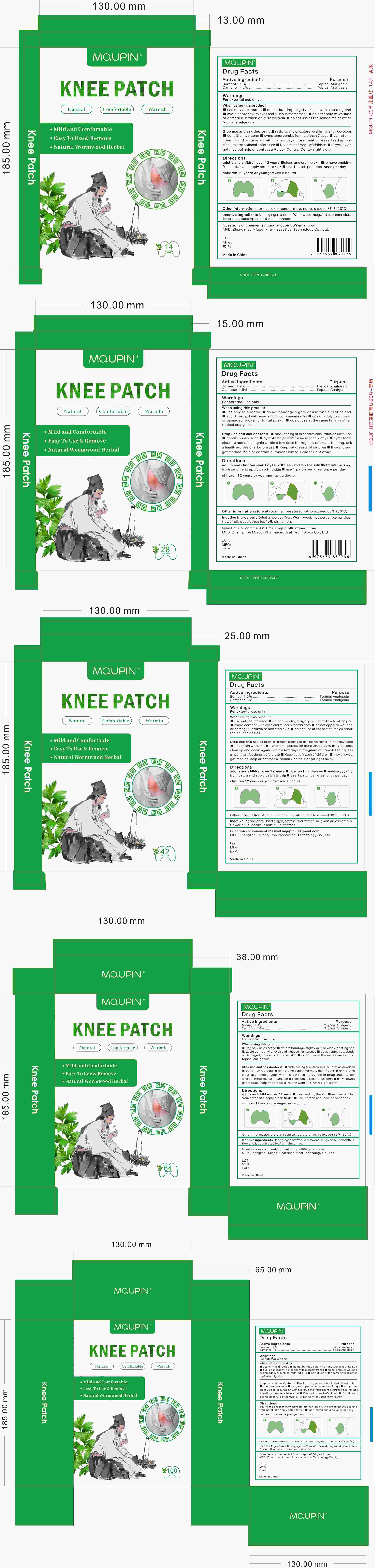 DRUG LABEL: Mqupin Knee Patch
NDC: 83781-002 | Form: PATCH
Manufacturer: Zhengzhou Miaoqi Pharmaceutical Technology Co., Ltd
Category: otc | Type: HUMAN OTC DRUG LABEL
Date: 20250508

ACTIVE INGREDIENTS: CAMPHOR (SYNTHETIC) 1.5 g/100 1; BORNEOL 1.2 g/100 1
INACTIVE INGREDIENTS: ARTEMISIA VULGARIS TOP OIL; CINNAMON; WORMWOOD; OSMANTHUS FRAGRANS FLOWER; EUCALYPTUS OIL; SAFFRON; GINGER

83781-002 Update V3 Update Pack

Active Ingredient

Borneol 1.2%
Camphor 1.5%

Purpose

Topical Analgesic

Use

temporarily relieves minor pain associated with:

■arthritis

■muscle strains

■sprains

■bruises

■ joint pain

Warnings

For external use only.

When Using

■ use only as directed

■ do not bandage tighty or use with a heating pad

■ avoid contact with eyes and mucous membranes

■ do not apply to wounds or damaged, broken or imitated skin

■ do not use at the same time as other topical analgesics

Stop Use

■ rash, itching or excessive skin irritation develops

■ condition worsens

■ symptoms persist for more than 7 days

■ symptoms clear up and occur again within a few days If pregnant or breastfeeding, ask a health professional before use

■ Keep out of reach of children

■ If swallowed, get medical help or contact a Poison Control Center right away

Ask Doctor

children 12 years or younger

Keep Out Of Reach Of Children

Directions

adults and children over 12 years:

■clean and dry the affected area

■remove backing from patch and apply patch to affected area

■use 1 patch per knee for 8 to 12 hours, once per day

Other information

store at room temperature, not to exceed 86°F (30°C)

Inactive ingredients

Dried ginger, saffron, Wormwood, mugwort oil, osmanthus flower oil, eucalyptus leaf oil, cinnamon.

Questions

mqupin86@gmail.com